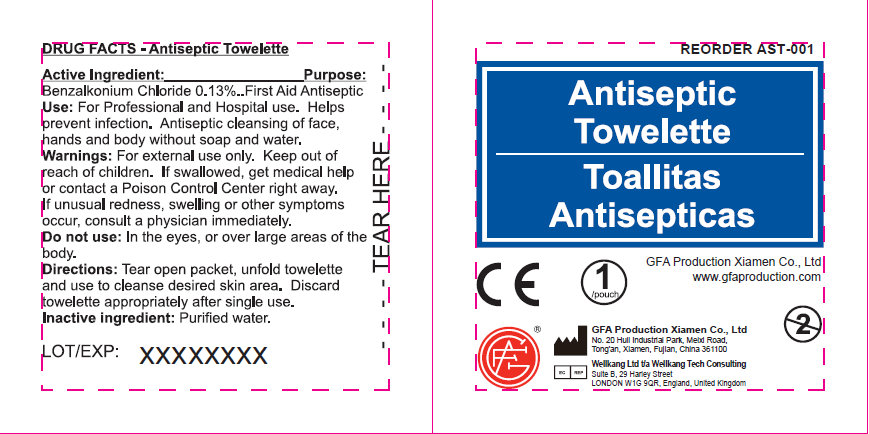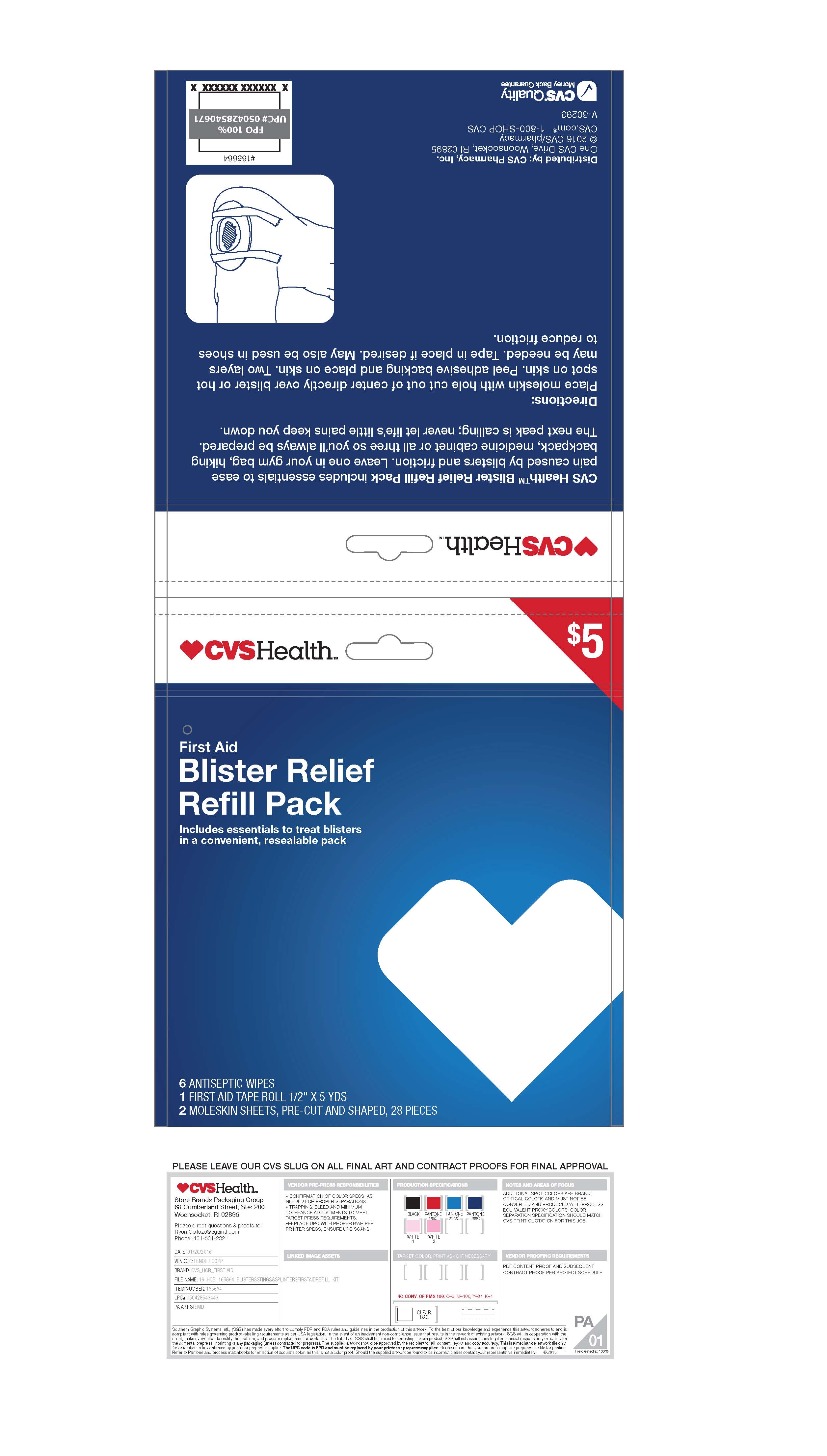 DRUG LABEL: CVS Blister Relief Refill Pack
NDC: 69842-406 | Form: KIT | Route: TOPICAL
Manufacturer: CVS
Category: otc | Type: HUMAN OTC DRUG LABEL
Date: 20161227

ACTIVE INGREDIENTS: BENZALKONIUM CHLORIDE 1.3 mg/1 mL
INACTIVE INGREDIENTS: WATER

CVS First Aid Blister Relief Refill Pack

Active Ingredient

Benzalkonium Chloride .13%

Purpose

First Aid Antiseptic

Use

For Professional and Hospital use. Helps prevent infection. Antiseptic cleansing of face, hands and body without soap and water.

Warnings

For external use only. Keep out of reach of children. If swallowed, get medical help or contact a Poison Control Center right away. If unusual redness, swelling or other symptoms occur, cunsult a physician immediately.

Do not use

In the eyes, or over large areas of the body

Directions

Tear open packet, unfold towelette and use to cleanse desired skin are. Discard towelette appropriately after single use

Inactive Ingredients

Purified Water

Antiseptic Towelette

GFA Production Xiamen Co., Ltd
www.gfaproduction.com